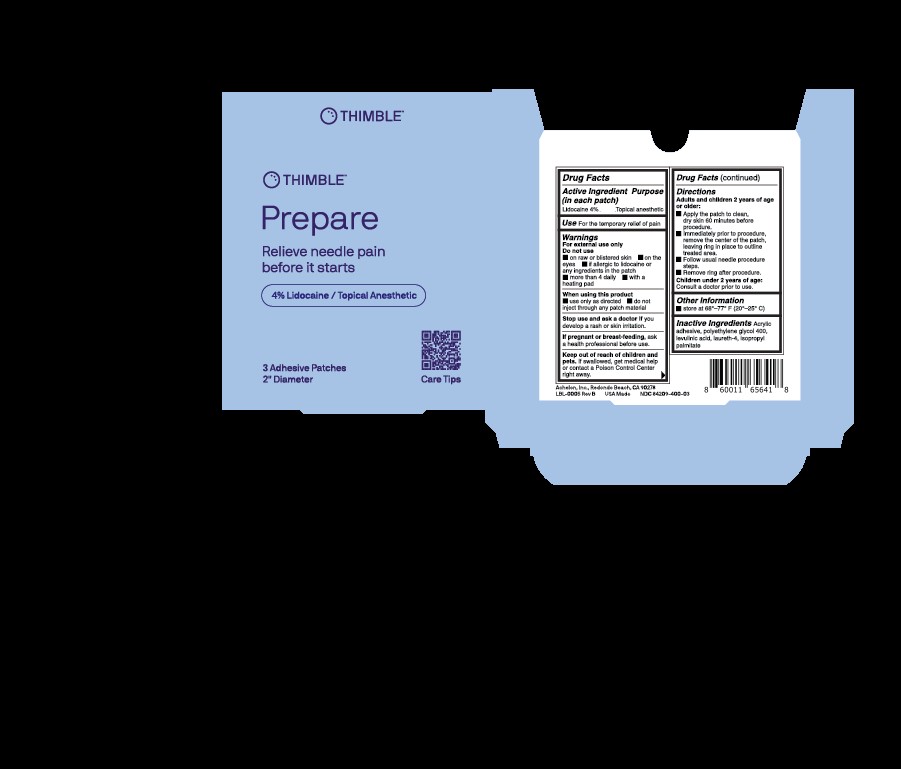 DRUG LABEL: Achelon Lidocaine Patch
NDC: 84209-400 | Form: PATCH
Manufacturer: Achelon, Inc
Category: otc | Type: HUMAN OTC DRUG LABEL
Date: 20250326

ACTIVE INGREDIENTS: LIDOCAINE 7.54 mg/60.81 cm2
INACTIVE INGREDIENTS: LEVULINIC ACID; ISOPROPYL PALMITATE; POLYETHYLENE GLYCOL 400; ACRYLIC ACID/ETHYLENE COPOLYMER (600 MPA.S)

Achelon Lidocaine 4% Patch

Active Ingredient

Lidocaine 4%

Purpose

Topical Analgesic

Inactive Ingredients

Propylene Glycol 400

Levulinic Acid

Brij L4 LQ

Isopropyl palmitate

Use

For the temporary relief of pain

Warnings

For external use only

Do not use

- on raw or blistered skin
- on the eyes
- if allergic to lidocaine or any ingredients in the patch
- more than 4 daily
- with a heating pad

When using this product

- use only as directed
- do not inject through any patch material

Stop use and ask a doctor if

If you develop a rash or skin irritation

If pregnant or breastfeeding

ask a health professional before use.

Keep out of reach of children and pets

if swallowed, get medical help or contact a Poison Control Center right away.

Directions

Adults and children 2 years of age or older:

- Apply the patch to clean, dry skin 60 minutes prior to procedure
- Immediately prior to procedure, remove the center of the patch, leaving ring in place to outline treated area
- Follow usual needle procedure steps
- Remove ring after procedure

Children under 2 years of age:

Consult a doctor prior to use